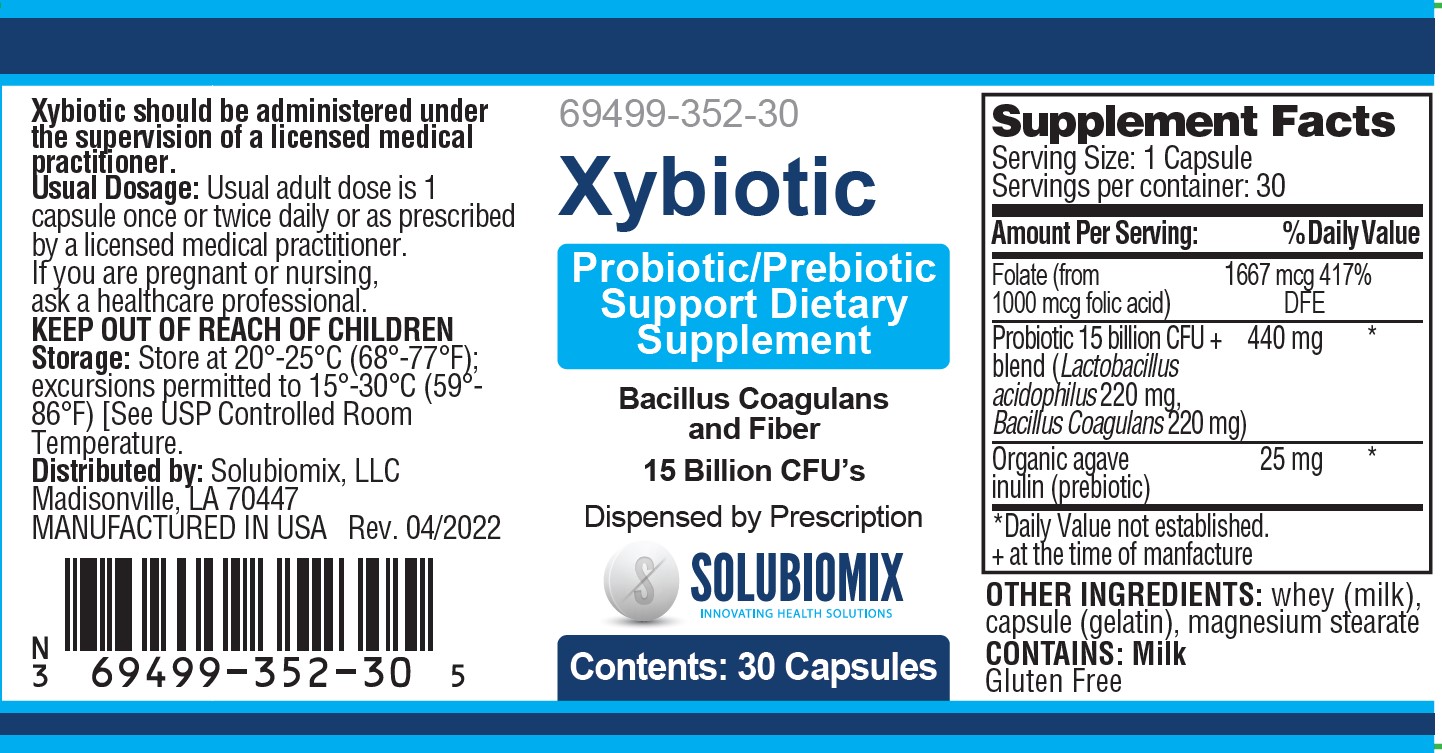 DRUG LABEL: Xybiotic
NDC: 69499-352 | Form: CAPSULE
Manufacturer: Solubiomix, LLC
Category: other | Type: DIETARY SUPPLEMENT
Date: 20251006

ACTIVE INGREDIENTS: BACILLUS COAGULANS 220 mg/1 1; INULIN 25 mg/1 1; FOLIC ACID 1 mg/1 1; LACTOBACILLUS ACIDOPHILUS 220 mg/1 1
INACTIVE INGREDIENTS: WHEY; GELATIN; MAGNESIUM STEARATE

Xybiotic

STATEMENT OF IDENTITY

XYBIOTIC Dietary Supplemement

Dispensed by Prescription

Serving Size: 1 Capsule Servings per container: 30
Amount Per Serving: |  | %DV
Folic Acid; Probiotic Blend; (Lactobacillus acidophilus 220 mg, Bacillus Coagulans 220 mg) | 1667 mcg DFE (1 mg); 15 Billion CFU | 417%; *
Dietary Fiber (as Inulin) | 25 mg | *
*Daily Values (DV) not established

OTHER INGEDIENTS: whey (milk), capsule (gelatin), magnesium stearate. CONTAINS: Milk
Gluten Free

XYBIOTIC is an orally administered prescription probiotic/prebiotic formulation for the clinical dietary management of suboptimal nutritional status in patients where advanced supplementation is required and nutritional supplementation in physiologically stressful conditions for maintenance of good health is needed.#

These statements have not been evaluated by the Food and Drug Administration. This product is not intended to diagnose, treat, cure or prevent disease.

XYBIOTIC is manufactured in accordance with Current Good Manufacturing Practice for foods, using ingredients that have been approved by the U.S. Food and Drug Administration (FDA) as food additives or are “Generally Recognized as Safe” (GRAS) for their intended use.

DOSAGE

Usual adult dose is 1 capsule once or twice daily, or as prescribed by a licensed medical practitioner.

If you are pregnant or nursing, ask a healthcare professional.

XYBIOTIC should be administered under the supervision of a licensed medical practitioner.‡

SAFE HANDLING

PRECAUTIONFolic acid in doses above 1 mg daily may obscure pernicious anemia in that hematologic remission can occur while neurological manifestations progress.† XYBIOTIC Capsules should only be used under the direction and supervision of a licensed medical practitioner.‡

This product is contraindicated in patients with a known hypersensitivity to any of the ingredients.

PROBICHEW chews should only be used under the direction and supervision of a licensed medical practitioner. Use with caution in patients that may have a medical condition, are pregnant, lactating, trying to conceive, under the age of 18, or taking medications.

KEEP OUT OF REACH OF CHILDREN

STORAGE:

Store at 20°-25°C (68°-77°F); excursions permitted to 15°-30°C (59°-86°F) [See USP Controlled Room Temperature.]

HOW SUPPLIED HEALTH CLAIM

PROBICHEW, Probiotic/Prebiotic Support

Dietary Supplement

Each bottles contains 30 Capsules (white) 69499-352-30#

Manufactured in USA for:

Solubiomix, LLC

Madisonville, LA 70447

Rev. 05/2022

# Solubiomix does not represent these product codesto be National Drug Codes (NDC). Product codes are formatted according to standard industry practice, to meet the formatting requirement by pedigree reporting and supply-chain control including pharmacies.

‡ This product is a prescription-folate with or without other dietary ingredients that – due to increased folate levels increased risk associated with masking of B12 deficiency (pernicious anemia) requires administration under the care of a licensed medical practitioner (61 FR 8760).1-3 The most appropriate way to ensure pedigree reporting consistent with these regulatory guidelines and safety monitoring is to dispense this product only by prescription.
†This is not an Orange Book product. This product may be administered only under a physician’s supervision and all prescriptions using this product shall be pursuant to state statutes as applicable. The ingredients, indication or claims of this product are not to be construed to be drug claims.
1. Federal Register Notice of August 2, 1973 (38 FR 20750)
2. Federal Register Notice of October 17, 1980 (45 FR 69043, 69044)
3. Federal Register Notice of March 5, 1996 (61 FR 8760)